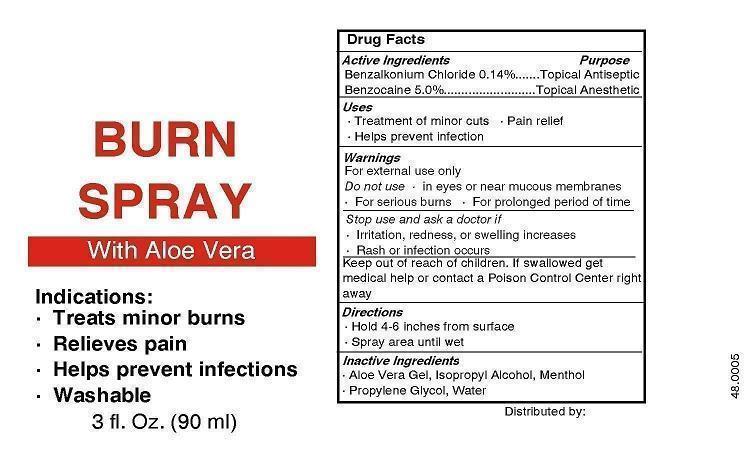 DRUG LABEL: Your Logo Here Burn First Aid
NDC: 52982-121 | Form: SPRAY, METERED
Manufacturer: Dixon Investments, Inc.
Category: otc | Type: HUMAN OTC DRUG LABEL
Date: 20130408

ACTIVE INGREDIENTS: BENZOCAINE 3825 mg/90 mL; BENZALKONIUM CHLORIDE 107.1 mg/90 mL
INACTIVE INGREDIENTS: ALOE VERA LEAF; ISOPROPYL ALCOHOL; MENTHOL; PROPYLENE GLYCOL; WATER

YOUR LOGO HERE BURN SPRAY WITH ALOE VERA

Active Ingredients

Benzalkonium Chloride 0.14%
Benzocaine 5.0%

Purpose

Topical Antiseptic
Topical Anesthetic

Uses

Treatment of minor cuts
Pain relief
Helps prevent infection

Warnings

For external use only

Do not use

in eyes or near mucous membranes
For serious burns
For prolonged period of time

Stop use and ask a doctor if

Irritation, redness, or swelling increases
Rash or infection occurs

Keep out of reach of children.

If swallowed get medical help or contact a Poison Control Center right away

Directions

Hold 4-6 inches from surface
Spray area until wet

Inactive Ingredients

Aloe Vera Gel, Isopropyl Alcohol, Menthol, Propylene Glycol, Water